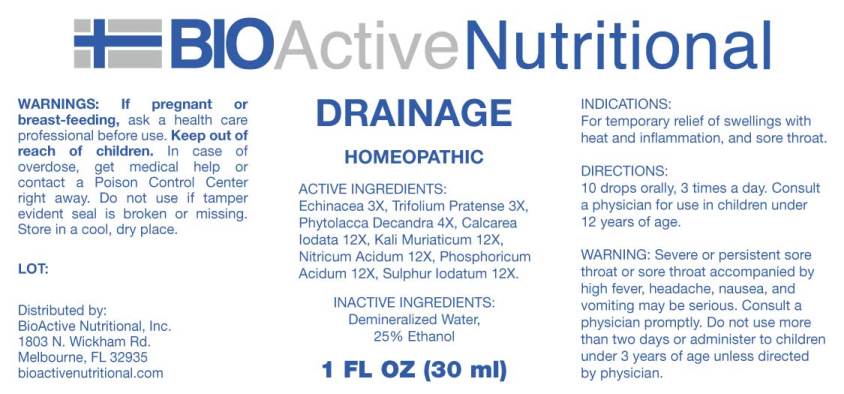 DRUG LABEL: Drainage
NDC: 43857-0489 | Form: LIQUID
Manufacturer: BioActive Nutritional, Inc.
Category: homeopathic | Type: HUMAN OTC DRUG LABEL
Date: 20240731

ACTIVE INGREDIENTS: ECHINACEA ANGUSTIFOLIA 3 [hp_X]/1 mL; TRIFOLIUM PRATENSE FLOWER 3 [hp_X]/1 mL; PHYTOLACCA AMERICANA ROOT 4 [hp_X]/1 mL; CALCIUM IODIDE 12 [hp_X]/1 mL; POTASSIUM CHLORIDE 12 [hp_X]/1 mL; NITRIC ACID 12 [hp_X]/1 mL; PHOSPHORIC ACID 12 [hp_X]/1 mL; SULFUR IODIDE 12 [hp_X]/1 mL
INACTIVE INGREDIENTS: WATER; ALCOHOL

Drug Facts:

ACTIVE INGREDIENTS:

Echinacea (Angustifolia) 3X, Trifolium Pratense 3X, Phytolacca Decandra 4X, Calcarea Iodata 12X, Kali Muriaticum 12X, Nitricum Acidum 12X, Phosphoricum Acidum 12X, Sulphur Iodatum 12X.

INDICATIONS:

For temporary relief of swellings with heat and inflammation, and sore throat.

WARNINGS:

If pregnant or breast-feeding, ask a health care professional before use.

Keep out of reach of children. In case of overdose, get medical help or contact a Poison Control Center right away.

Do not use if tamper evident seal is broken or missing.

Store in cool, dry place.

WARNING: Severe or persistent sore throat or sore throat accompanied by high fever, headache, nausea, and vomiting may be serious. Consult a physician promptly. Do not use more than two days or administer to children under 3 years of age unless directed by physician.

Keep out of reach of children. In case of overdose, get medical help or contact a Poison Control Center right away.

DIRECTIONS:

10 drops orally, 3 times a day. Consult a physician for use in children under 12 years of age.

INDICATIONS:

For temporary relief of swellings with heat and inflammation, and sore throat.

INACTIVE INGREDIENTS:

Demineralized Water, 25% Ethanol

QUESTIONS:

Distributed by:
BioActive Nutritional, Inc.
1803 N. Wickham Rd.
Melbourne, FL 32935
bioactivenutritional.com

PACKAGE LABEL DISPLAY:

BIOActive Nutritional

DRAINAGE

HOMEOPATHIC

1 FL OZ (30 ml)